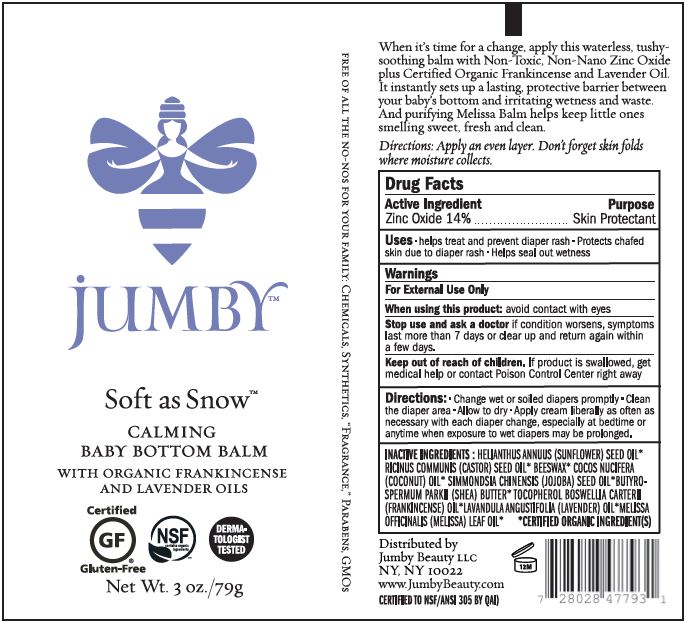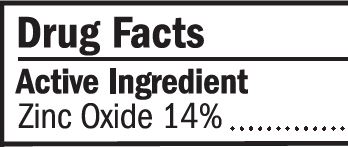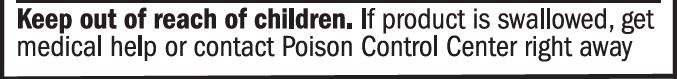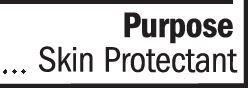 DRUG LABEL: Diaper Cream
NDC: 62932-233 | Form: OINTMENT
Manufacturer: Private Label Select Ltd CO
Category: otc | Type: HUMAN OTC DRUG LABEL
Date: 20201229

ACTIVE INGREDIENTS: ZINC OXIDE 14 g/100 g
INACTIVE INGREDIENTS: WHITE WAX; SHEA BUTTER; LEMON BALM OIL; LAVENDER OIL; FRANKINCENSE OIL; .BETA.-TOCOPHEROL; .GAMMA.-TOCOPHEROL; MELISSA OFFICINALIS LEAF OIL; CASTOR OIL; JOJOBA OIL; COCONUT OIL; SUNFLOWER OIL; .ALPHA.-TOCOPHEROL, D-; .DELTA.-TOCOPHEROL

Jumby Soft as Snow, Calming Baby Bottom Balm